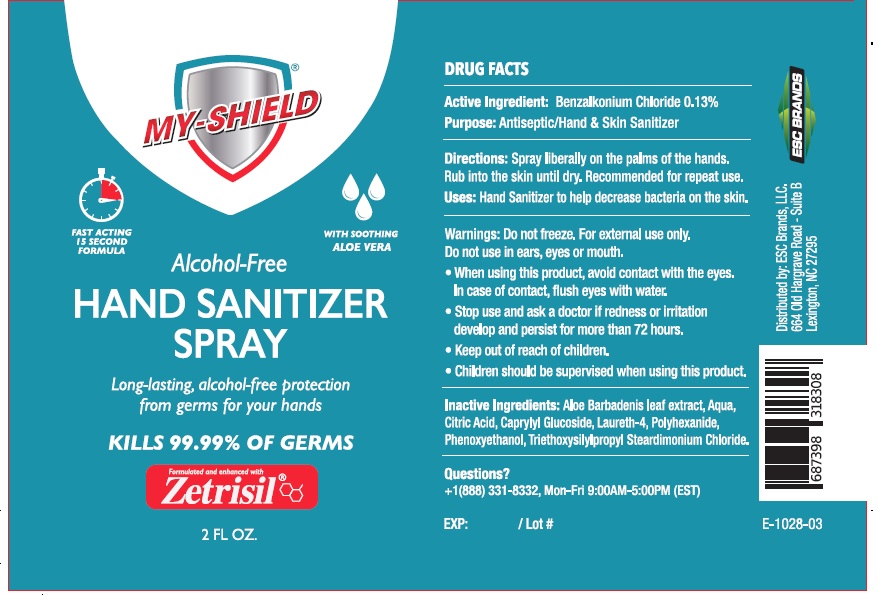 DRUG LABEL: My-Shield Hand Sanitizer
NDC: 71884-012 | Form: SPRAY
Manufacturer: Enviro Specialty Chemicals Inc
Category: otc | Type: HUMAN OTC DRUG LABEL
Date: 20241231

ACTIVE INGREDIENTS: BENZALKONIUM CHLORIDE 0.13 g/100 mL
INACTIVE INGREDIENTS: ALOE VERA LEAF; WATER; CITRIC ACID MONOHYDRATE; CAPRYLYL GLUCOSIDE; LAURETH-4; POLIHEXANIDE; PHENOXYETHANOL; TRIETHOXYSILYLPROPYL STEARDIMONIUM CHLORIDE

MY-SHIELD HAND SANITIZER SPRAY

Active Ingredient:

Benzalkonium Chloride 0.13%

Purpose:

Antiseptic/Hand & Skin Sanitizer

Uses:

Hand Sanitizer to help decrease bacteria on the skin.

Directions:

Spray liberally on the palms of the hands.

Rub into skin until dry. Recommended for repeat use

Warnings:

Do not freeze. For external use only.

Do not use in ears, eyes or mouth.

- When using this product, avoid contact with eyes. In case of contact, flush eyes with water.
- Stop use and ask a doctor if redness or irritation develop and persist for more than 72 hours.

- Keep out of reach of children.
- Children should be supervised when using this product.

Inactive Ingredients:

Aloe Barbadensis leaf extract, Aqua, Citric Acid, Caprylyl Glucoside, Laureth-4, Polyhexanide, Phenoxyethanol, Triethoxysilylpropyl Steardimonium Chloride.

Questions?

+1(888) 331-8332, Mon-Fri 9:00AM-5:00PM (EST)

FAST ACTING 15 SECOND FORMULA

WITH SOOTHING ALOE VERA

Alcohol-Free

Long-lasting, alcohol-free protection from germs for your hands

KILLS 99.99% OF GERMS

Formulated and enhanced with Zetrisil

Distributed by: ESC Brands, LLC.

664 Old Hargraves Road - Suite B

Lexington, NC 27295